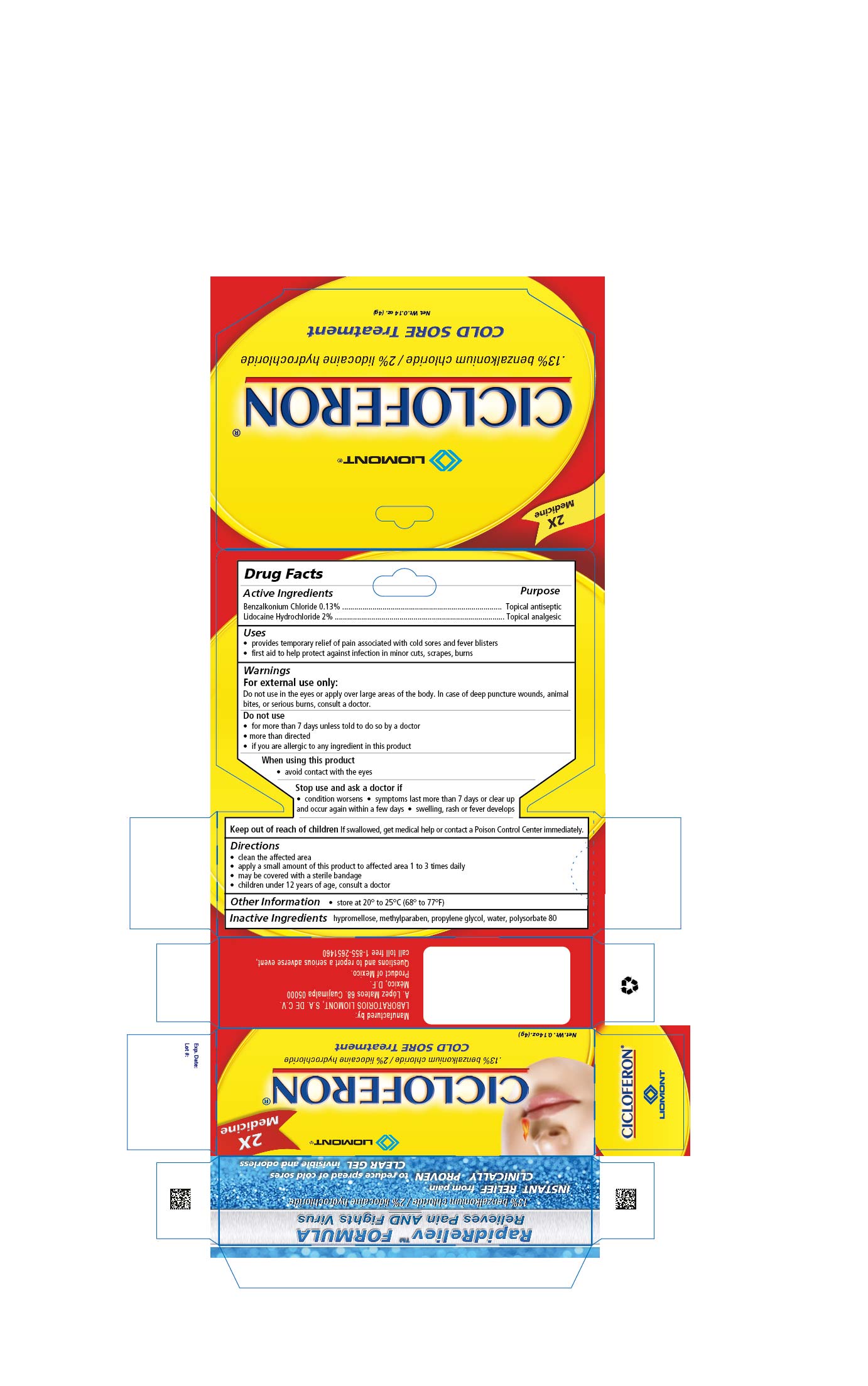 DRUG LABEL: CICLOFERON
NDC: 59208-002 | Form: GEL
Manufacturer: Laboratorios Liomont, S.A. de C.V.
Category: otc | Type: HUMAN OTC DRUG LABEL
Date: 20241017

ACTIVE INGREDIENTS: BENZALKONIUM CHLORIDE 1.3 mg/1 g; LIDOCAINE HYDROCHLORIDE 20 mg/1 g
INACTIVE INGREDIENTS: HYPROMELLOSE, UNSPECIFIED; METHYLPARABEN; PROPYLENE GLYCOL; WATER; POLYSORBATE 80

CiclofrnGel

Active Ingredients

Benzalkonium Chloride 0.13%

Lidocaine Hydrchloride 2%

Purpose

Topical antiseptic

Topical analgesic

Uses

- provides temporary relief of pain associated with cold sores and fever blisters
  - first aid to help protect against infection in minor cuts, scrapes, burns

Warnings

For external use only:

Do not use in the eyes or apply over large areas of the body. In case of deep puncture wounds, animal bites, or serious burns, consult a doctor.

Do not use

- for more than 7 days unless told to do so by a doctor
- more than directed
- if you are allergic to any ingredient in this product

When using this product

- avoid contact with the eyes

Keep out of reach of children

If swallowed, get medical help or contact a Poison Control Center immediately.

Directions

- clean the affected area
- apply a small amount of this product to the affected area 1 to 3 times daily
- may be covered with a sterile bandage
- children under 12 years of age, consult a doctor

Other Information

- store at 20° to 25°C (68° to 77°F)

Inactive Ingredients

hypromellose, methylparaben, propylene glycol, water, polysorbate 80